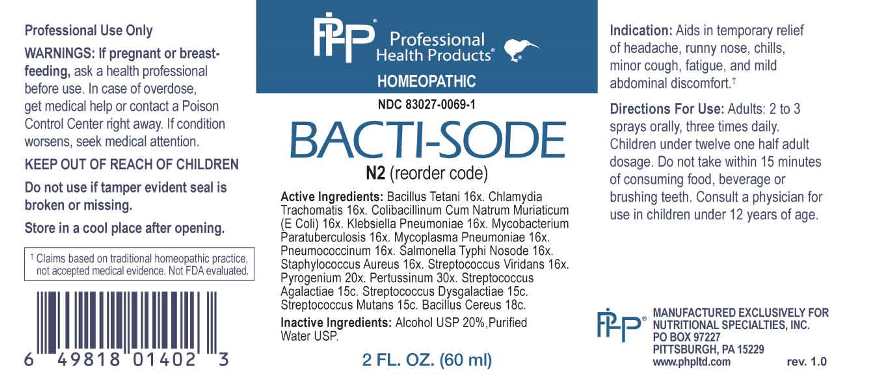 DRUG LABEL: Bacti Sode
NDC: 83027-0069 | Form: SPRAY
Manufacturer: Nutritional Specialties, Inc.
Category: homeopathic | Type: HUMAN OTC DRUG LABEL
Date: 20250521

ACTIVE INGREDIENTS: CLOSTRIDIUM TETANI 16 [hp_X]/1 mL; CHLAMYDIA TRACHOMATIS 16 [hp_X]/1 mL; ESCHERICHIA COLI 16 [hp_X]/1 mL; KLEBSIELLA PNEUMONIAE 16 [hp_X]/1 mL; MYCOBACTERIUM AVIUM SUBSP. PARATUBERCULOSIS 16 [hp_X]/1 mL; MYCOPLASMA PNEUMONIAE 16 [hp_X]/1 mL; STREPTOCOCCUS PNEUMONIAE 16 [hp_X]/1 mL; SALMONELLA ENTERICA ENTERICA SEROVAR TYPHI 16 [hp_X]/1 mL; STAPHYLOCOCCUS AUREUS 16 [hp_X]/1 mL; STREPTOCOCCUS VIRIDANS GROUP 16 [hp_X]/1 mL; RANCID BEEF 20 [hp_X]/1 mL; HUMAN SPUTUM, BORDETELLA PERTUSSIS INFECTED 30 [hp_X]/1 mL; STREPTOCOCCUS AGALACTIAE 15 [hp_C]/1 mL; STREPTOCOCCUS DYSGALACTIAE 15 [hp_C]/1 mL; STREPTOCOCCUS MUTANS 15 [hp_C]/1 mL; BACILLUS CEREUS 18 [hp_C]/1 mL
INACTIVE INGREDIENTS: WATER; ALCOHOL

DRUG FACTS:

ACTIVE INGREDIENTS:

Bacillus Tetani 16X, Chlamydia Trachomatis 16X, Colibacillinum Cum Natrum Muriaticum (e Coli) 16X, Klebsiella Pneumoniae 16X, Mycobacterium Paratuberculosis 16X, Mycoplasma Pneumoniae 16X, Pneumococcinum 16X, Salmonella Typhi Nosode 16X, Staphylococcus Aureus 16X, Streptococcus Viridans 16X, Pyrogenium 20X, Pertussinum 30X, Streptococcus Agalactiae 15C, Streptococcus Dysgalactiae 15C, Streptococcus Mutans 15C, Bacillus Cereus 18C.

PURPOSE:

Aids in temporary relief of headache, runny nose, chills, minor cough, fatigue, and mild abdominal discomfort.†

†Claims based on traditional homeopathic practice, not accepted medical evidence. Not FDA evaluated.

WARNINGS:

Professional Use Only

If pregnant or breast-feeding, ask a health professional before use.

In case of overdose, get medical help or contact a Poison Control Center right away.

If condition worsens, seek medical attention.

KEEP OUT OF REACH OF CHILDREN

Do not use if tamper evident seal is broken or missing.

Store in a cool place after opening

KEEP OUT OF REACH OF CHILDREN:

In case of overdose, get medical help or contact a Poison Control Center right away.

DIRECTIONS:

Adults: 2 to 3 sprays orally, three times daily. Children under twelve one half adult dosage. Do not take within 15 minutes of consuming food, beverage or brushing teeth. Consult a physician for use in children under 12 years of age.

INDICATIONS:

Aids in temporary relief of headache, runny nose, chills, minor cough, fatigue, and mild abdominal discomfort.†

†Claims based on traditional homeopathic practice, not accepted medical evidence. Not FDA evaluated.

INACTIVE INGREDIENTS:

Alcohol USP 20%, Purified Water USP.

QUESTIONS:

MANUFACTURED EXCLUSIVELY FOR

NUTRITIONAL SPECIALTIES, INC.

PO BOX 97227

PITTSBURG, PA 15229

www.phpltd.com

PACKAGE LABEL DISPLAY:

Professional

Health Products

HOMEOPATHIC

NDC 83027-0069-1

BACTI-SODE

2 FL. OZ (60 ml)